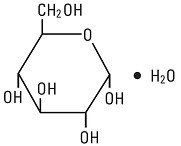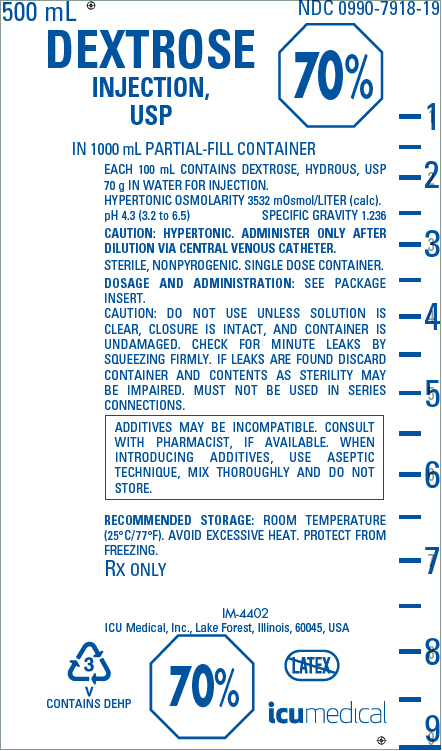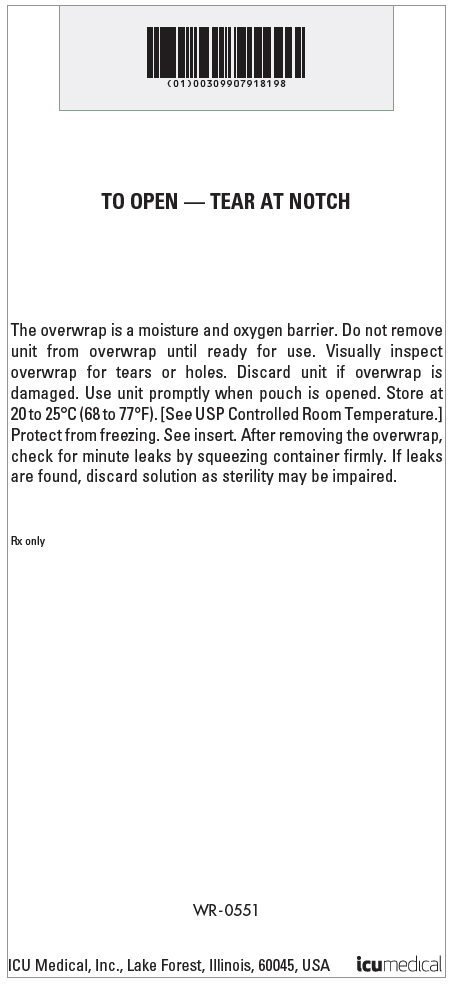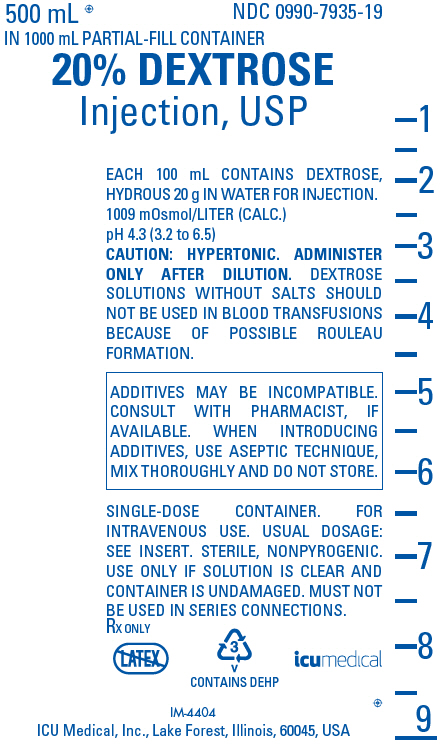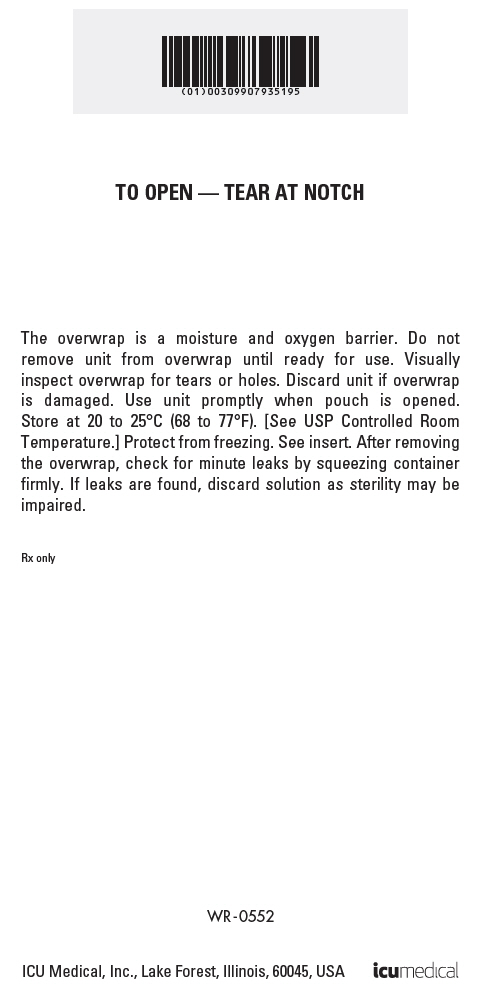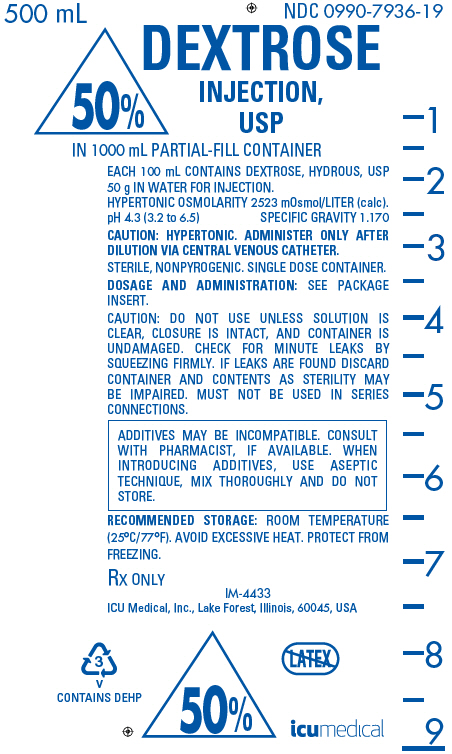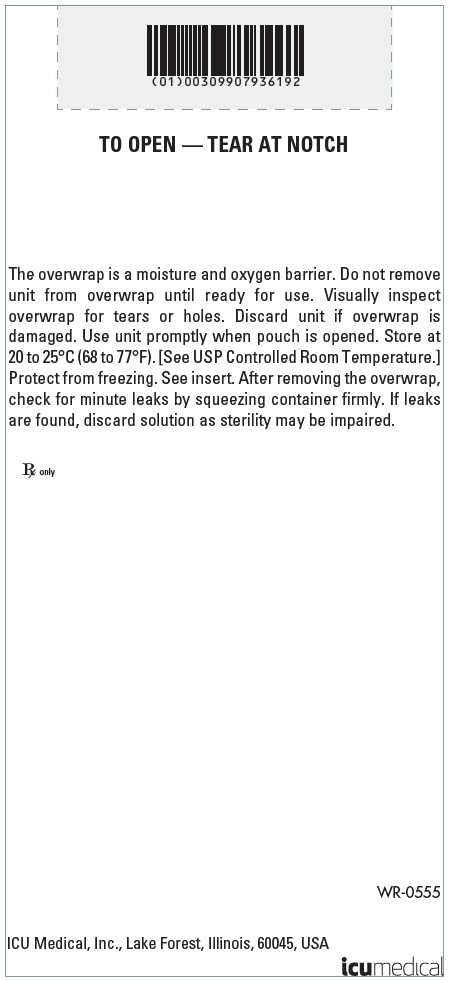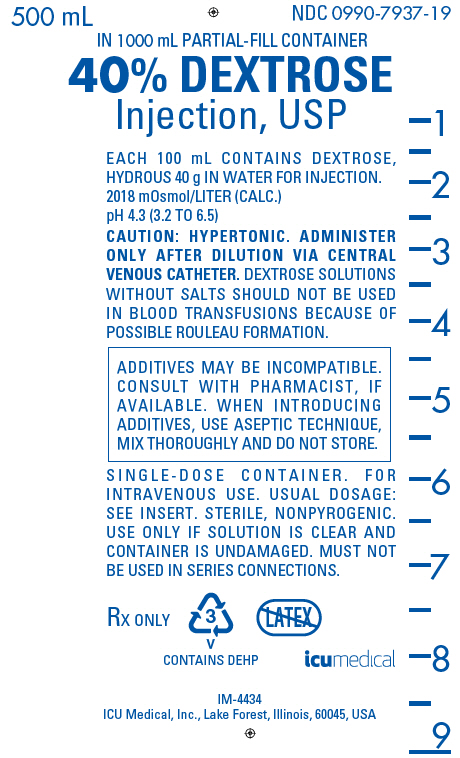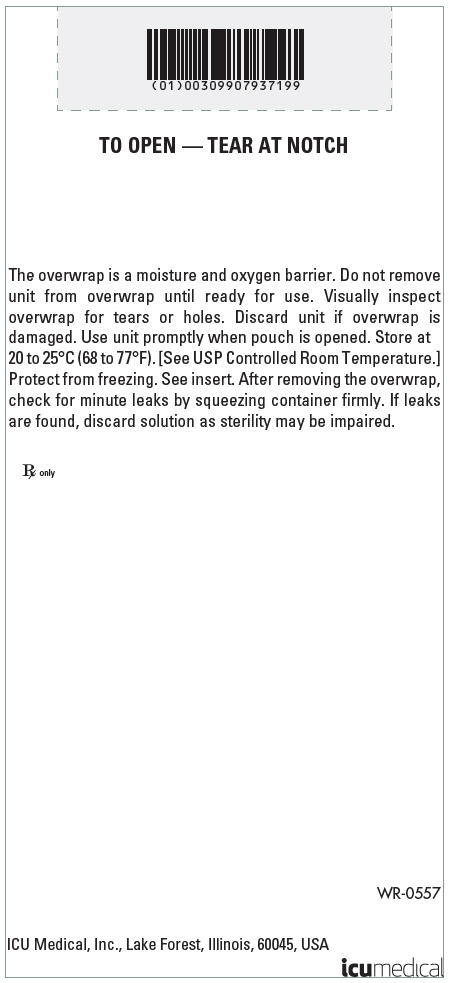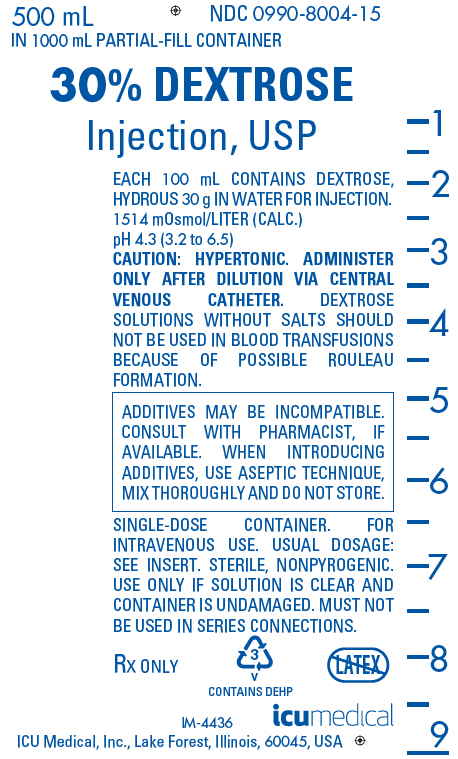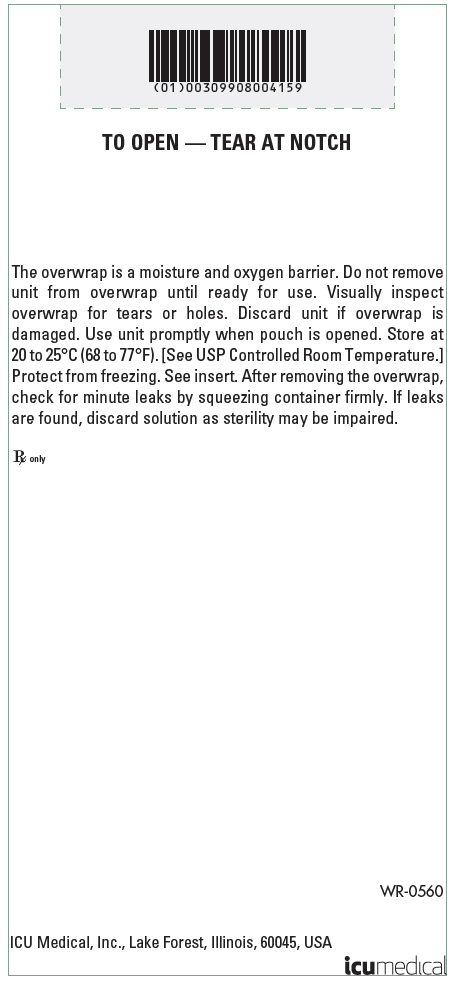 DRUG LABEL: Dextrose
NDC: 0990-7918 | Form: INJECTION, SOLUTION
Manufacturer: ICU Medical Inc.
Category: prescription | Type: HUMAN PRESCRIPTION DRUG LABEL
Date: 20251102

ACTIVE INGREDIENTS: DEXTROSE MONOHYDRATE 70 g/100 mL
INACTIVE INGREDIENTS: WATER

HIGHLIGHTS OF PRESCRIBING INFORMATION

These highlights do not include all the information needed to use DEXTROSE INJECTION 20%, 30%, 40%, 50% and 70% safely and effectively. See full prescribing information for DEXTROSE INJECTION 20%, 30%, 40%, 50% and 70%.
DEXTROSE injection, for intravenous use
Initial U.S. Approval: 1940

1 INDICATIONS AND USAGE

Dextrose Injection 20%, 30%, 40%, 50% and 70%, mixed with amino acids or other compatible intravenous fluids, is indicated as a source of calories for patients requiring parenteral nutrition when oral or enteral nutrition is not possible, insufficient or contraindicated (1)

2 DOSAGE AND ADMINISTRATION

- Must be diluted with compatible intravenous fluids or used as admixture, prior to administration. Not for direct intravenous infusion. (2.1)
- Only for slow intravenous infusion only into a: (2.1)
  - Central vein, if final dextrose concentration is greater than 5% or osmolality is greater than 900 mOsm/L
  - Peripheral vein, if final dextrose concentration 5% or less and osmolality is less than 900 mOsm/L
- Individualize dosage based on the patient's clinical condition, body weight, nutritional/fluid requirements, as well as additional energy given orally/enterally (2.2)
- Discontinue infusion of concentrated dextrose solutions slowly and/or administer 5% dextrose (2.3)

3 DOSAGE FORMS AND STRENGTHS

Injection: Single-dose, partial-fill, flexible containers with (3):

500 mL fill volume in 1000 mL flexible container:

- 20% (0.2 grams/mL): 20 grams of dextrose hydrous per 100 mL
- 30% (0.3 grams/mL): 30 grams of dextrose hydrous per 100 mL
- 40% (0.4 grams/mL): 40 grams of dextrose hydrous per 100 mL
- 50% (0.5 grams/mL): 50 grams of dextrose hydrous per 100 mL
- 70% (0.7 grams/mL): 70 grams of dextrose hydrous per 100 mL

4 CONTRAINDICATIONS

- Severe dehydration (4)
- Known hypersensitivity to dextrose (4)

5 WARNINGS AND PRECAUTIONS

- Hyperglycemia or Hyperosmolar Hyperglycemic State: Monitor blood glucose and administer insulin as needed (5.1)
- Hypersensitivity Reactions: Monitor for signs and symptoms and discontinue infusion if reactions occur (5.2)
- Risk of Infection: Monitor for signs and symptoms and laboratory parameters (5.3)
- Refeeding Syndrome: Monitory laboratory parameters (5.4)
- Vein Damage and Thrombosis: Administer solutions containing more than 5% dextrose as the final concentration or solutions with an osmolarity ≥ 900 mOsm/L through a central vein (2.1, 5.5)
- Aluminum Toxicity: Dextrose Injection contains aluminum that may be toxic. Patients with impaired renal function, and preterm infants, at higher risk. Limit aluminum to less than 4 mcg/kg/day (5.6, 8.4)
- Parenteral Nutrition Associated Liver Disease: increased risk in patients who receive parenteral nutrition for extended periods of time, especially preterm infants; monitor liver function tests, if abnormalities occur consider discontinuation or dosage reduction. (5.7, 8.4)
- Electrolyte Imbalance and Fluid Overload: monitor daily fluid balance, blood electrolyte levels, correct as needed. (5.8, 8.4)

6 ADVERSE REACTIONS

The most common adverse reactions are hyperosmolar syndrome, infection both systemic and at the injection site, vein thrombosis or phlebitis, and hypervolemia. (6)

To report SUSPECTED ADVERSE REACTIONS, contact ICU Medical, Inc. at 1-800-441-4100, or FDA at 1-800-FDA-1088 or www.fda.gov/medwatch.

8 USE IN SPECIFIC POPULATIONS

Pediatric Use: Increased risk of hypoglycemia/hyperglycemia; monitor serum glucose concentrations. (8.4)

FULL PRESCRIBING INFORMATION

1 INDICATIONS AND USAGE

Dextrose Injection 20%, 30%, 40%, 50% and 70%, mixed with amino acids or other compatible intravenous fluids, is indicated as a source of calories for patients requiring parenteral nutrition when oral or enteral nutrition is not possible, insufficient, or contraindicated.

2 DOSAGE AND ADMINISTRATION

2.1 Important Preparation and Administration Instructions

Dextrose Injection is supplied in the following five strengths: 20%, 30%, 40%, 50% and 70% [see How Supplied/Storage and Handling (16)]. Prior to administration, Dextrose Injection must be diluted with other compatible intravenous fluids or used as an admixture with amino acids. It is not for direct intravenous infusion.

Preparation Prior to Administration

- Because additives may be incompatible, evaluate all additions to the plastic container for compatibility and stability of the resulting preparation. Consult with a pharmacist, if available. If it is deemed advisable to introduce additives, use aseptic technique and mix thoroughly.
- Inspect Dextrose Injection to ensure precipitates have not formed during the mixing or addition of additives. Discard the bag if precipitates are observed. Some opacity of the plastic container (due to moisture absorption during sterilization process) may be observed. This is normal and does not affect the solution quality or safety. The opacity will diminish gradually.
- Use promptly after admixing or dilution.
- For single use only; discard unused portion

Important Administration Instructions

- Set the vent to the closed position on a vented intravenous administration set to prevent air embolism.
- Use a dedicated line without any connections to avoid air embolism.
- Prior to infusion, visually inspect the diluted dextrose solution for particulate matter. The solution should be clear and there should be no precipitates. Do not administer unless solution is clear and container is undamaged.
- The choice of a central or peripheral venous route of infusion should depend on the osmolarity of the final infusate. Solutions with greater than 5% dextrose or with osmolarity of greater than or equal to 900 mOsm/L must be infused through a central catheter [see Warnings and Precautions (5.5)].

2.2 Dosing Information

Caution: Dextrose Injection is not for direct intravenous infusion. Prior to administration, Dextrose Injection must be diluted with other compatible intravenous fluids or used as an admixture with amino acids.

Individualize the dosage of Dextrose Injection based on the patient's clinical condition (ability to adequately metabolize dextrose), body weight, nutritional and fluid requirements, as well as additional energy given orally or enterally to the patient.

The administration rate should be governed, especially during the first few day of therapy, by the patient's tolerance to dextrose. Daily intake of amino acids and dextrose should be increased gradually to the maximum required dose as indicated by frequent determinations of blood glucose levels.

2.3 Discontinuation of Dextrose Injection

To reduce the risk of hypoglycemia, a gradual decrease in flow rate in the last hour of infusion should be considered.

3 DOSAGE FORMS AND STRENGTHS

Dextrose Injection 20%, 30%, 40%, 50%, and 70% USP are sterile, non-pyrogenic, hypertonic solutions of dextrose in single-dose, partial-fill, flexible containers.

500 mL fill volume in 1000 mL flexible container

- 20% (0.2 grams/mL): 20 grams of dextrose hydrous per 100 mL
- 30% (0.3 grams/mL): 30 grams of dextrose hydrous per 100 mL
- 40% (0.4 grams/mL): 40 grams of dextrose hydrous per 100 mL
- 50% (0.5 grams/mL): 50 grams of dextrose hydrous per 100 mL
- 70% (0.7 grams/mL): 70 grams of dextrose hydrous per 100 mL

4 CONTRAINDICATIONS

The use of Dextrose Injection is contraindicated in patients:

- who are severely dehydrated as hypertonic dextrose solution can worsen the patient's hyperosmolar state.
- with known hypersensitivity to dextrose [see Warnings and Precautions (5.2)].

5 WARNINGS AND PRECAUTIONS

5.1 Hyperglycemia and Hyperosmolar Hyperglycemic State

The use of dextrose infusions in patients with diabetes mellitus or impaired glucose tolerance may worsen hyperglycemia. Administration of dextrose at a rate exceeding the patient's utilization rate may lead to hyperglycemia, coma, and death. Patients with underlying confusion and renal impairment who receive dextrose infusions, may be at greater risk of developing hyperosmolar hyperglycemic state. Monitor blood glucose levels and treat hyperglycemia to maintain optimum levels while administering Dextrose Injection. Insulin may be administered or adjusted to maintain optimal blood glucose levels during Dextrose Injection administration.

5.2 Hypersensitivity Reactions

Hypersensitivity reactions including anaphylaxis have been reported with dextrose infusions. Stop infusion immediately and treat patient accordingly if signs or symptoms of a hypersensitivity reaction develop. Signs or symptoms may include: tachypnea, dyspnea, hypoxia, bronchospasm, tachycardia, hypotension, cyanosis, vomiting, nausea, headache, sweating, dizziness, altered mentation, flushing, rash, urticaria, erythema, pyrexia, and chills.

5.3 Risk of Infections

Patients who require parenteral nutrition are at high risk of infections because the nutritional components of these solutions can support microbial growth. The risk of infection is increased in patients with malnutrition-associated immunosuppression, hyperglycemia exacerbated by dextrose infusion, long-term use and poor maintenance of intravenous catheters, or immunosuppressive effects of other concomitant conditions, drugs, or other components of the parenteral formulation (e.g., lipid emulsion).

To decrease the risk of infectious complications, ensure aseptic technique in catheter placement and maintenance, as well as aseptic technique in the preparation and administration of the nutritional formula.

Monitor for signs and symptoms (including fever and chills) of early infections, including laboratory test results (including leukocytosis and hyperglycemia) and frequent checks of the parenteral access device and insertion site for edema, redness and discharge.

5.4 Refeeding Syndrome

Refeeding severely undernourished patients may result in refeeding syndrome, characterized by the intracellular shift of potassium, phosphorus, and magnesium as the patient becomes anabolic. Thiamine deficiency and fluid retention may also develop. To prevent these complications, monitor severely undernourished patients and slowly increase nutrient intakes.

5.5 Vein Damage and Thrombosis

Dextrose Injection is for admixture with amino acids or dilution with other compatible intravenous fluids. It is not for direct intravenous infusion. Administer solutions containing more than 5% dextrose or with an osmolarity of ≥ 900 mOsm/L through a central vein [see Dosage and Administration (2.1)]. The infusion of hypertonic solutions into a peripheral vein may result in vein irritation, vein damage, and/or thrombosis. The primary complication of peripheral access is venous thrombophlebitis, which manifests as pain, erythema, tenderness or a palpable cord. Remove the catheter as soon as possible, if thrombophlebitis develops.

5.6 Aluminum Toxicity

Dextrose Injection contains no more than 25 mcg/L of aluminum. However, with prolonged parenteral administration in patients with renal impairment, the aluminum contained in Dextrose Injection may reach toxic levels. Preterm infants are at greater risk because their kidneys are immature, and they require large amounts of concomitant calcium and phosphate solutions that contain aluminum. Patients with renal impairment, including preterm infants, who receive parenteral levels of aluminum at greater than 4 to 5 mcg/kg/day, accumulate aluminum at levels associated with central nervous system and bone toxicity. Tissue loading may occur at even lower rates of administration of total parenteral nutrition products.

5.7 Risk of Parenteral Nutrition Associated Liver Disease

Parenteral Nutrition Associated Liver Disease (PNALD) has been reported in patients who receive parenteral nutrition for extended periods of time, especially preterm infants, and can present as cholestasis or steatohepatitis. The exact etiology is not entirely clear and is likely multifactorial. If Dextrose Injection-treated patients develop abnormal liver function tests consider discontinuation or dosage reduction.

5.8 Electrolyte Imbalance and Fluid Overload

Electrolyte deficits, particularly in serum potassium and phosphate, may occur during prolonged use of concentrated dextrose solutions.

Depending on the volume and rate of infusion, the intravenous administration of concentrated dextrose solutions can cause fluid and/or solute overloading resulting in dilution of serum electrolyte concentrations, overhydration, congested states or pulmonary edema. The risk of dilutional states is inversely proportional to the electrolyte concentrations in the administered solution. The risk of solute overload causing congested states with peripheral and pulmonary edema is directly proportional to the electrolyte concentrations in the solution.

Monitor blood electrolyte levels, correct fluid and electrolyte imbalances, and administer essential vitamins and minerals as needed. Monitor daily fluid balance.

6 ADVERSE REACTIONS

The following adverse reactions from voluntary reports or clinical studies have been reported with Dextrose Injection. Because many of these reactions were reported voluntarily from a population of uncertain size, it is not always possible to reliably estimate their frequency or establish a causal relationship to drug exposure.

- Hyperglycemia and hyperosmolar hyperglycemic state [see Warnings and Precautions (5.1)].
- Hypersensitivity reactions [see Warnings and Precautions (5.2)].
- Risk of infections [see Warnings and Precautions (5.3)].
- Refeeding syndrome [see Warnings and Precautions (5.4)].
- Vein damage and thrombosis [see Warnings and Precautions (5.5)].
- Aluminum toxicity [see Warnings and Precautions (5.6)].
- Risk of parenteral nutrition associated liver disease [see Warnings and Precautions (5.7)].
- Electrolyte imbalance and fluid overload [see Warnings and Precautions (5.8)].

8 USE IN SPECIFIC POPULATIONS

8.1 Pregnancy

Risk Summary

There are no data with Dextrose Injection in pregnant women. In addition, animal reproduction studies have not been conducted with dextrose. In the U.S. general population, the estimated background risk of major birth defects and miscarriage in clinically recognized pregnancies is 2 to 4% and 15 to 20%, respectively.

Clinical Considerations

Disease-Associated Maternal and/or Embryo/Fetal Risk

Consider parenteral nutrition in cases of severe maternal malnutrition where nutritional requirements cannot be fulfilled by the enteral route because of the risks to the fetus associated with severe malnutrition, including preterm delivery, low birth weight, intrauterine growth restriction, congenital malformations, and perinatal mortality.

8.2 Lactation

There are no data regarding the presence of dextrose in human milk, the effects on a breastfed infant, or the effects on milk production. The developmental and health benefits of breastfeeding should be considered along with the mother's clinical need for Dextrose Injection and any potential adverse effects on the breastfed infant from Dextrose Injection or from the underlying maternal condition.

8.4 Pediatric Use

Neonates, especially those born premature and with low birth weight are at increased risk of developing hypo – or hyperglycemia and therefore need close monitoring during treatment with intravenous glucose infusions to ensure adequate glycemic control in order to avoid potential long term adverse effects. Hypoglycemia in the newborn can cause prolonged seizures, coma and brain damage. Hyperglycemia has been associated with intraventricular hemorrhage, late onset bacterial and fungal infection, retinopathy of prematurity, necrotizing enterocolitis, bronchopulmonary dysplasia, prolonged length of hospital stay, and death. Plasma electrolyte concentrations should be closely monitored in the pediatric population as this population may have impaired ability to regulate fluids and electrolytes. In very low birth weight infants, excessive or rapid administration of Dextrose Injection may result in increased serum osmolality and possible intracerebral hemorrhage.

Because of immature renal function, preterm infants receiving prolonged treatment with Dextrose Injection, may be at risk aluminum toxicity [see Warnings and Precautions (5.6)].

Patients, including pediatric patients, may be at risk for Parenteral Nutrition Associated Liver Disease (PNALD) [see Warnings and Precautions (5.7)].

8.5 Geriatric Use

Clinical studies of Dextrose Injection did not include sufficient numbers of patients aged 65 and over to determine whether they respond differently from other younger patients. Other reported clinical experience has not identified differences in responses between the elderly and younger patients.

10 OVERDOSAGE

An increased infusion rate of Dextrose Injection or administration of a concentrated dextrose solution can cause hyperglycemia, hyperosmolality, and adverse effects on water and electrolyte balance [see Warnings and Precautions (5.1, 5.8)].

Severe hyperglycemia and severe dilutional hyponatremia, and their complications, can be fatal.

Discontinue infusion and institute appropriate corrective measures in the event of overhydration or solute overload during therapy, with particular attention to respiratory and cardiovascular systems.

For current information on the management of poisoning or overdosage, contact the National Poison Control Center at 1-800-222-1222 or www.poison.org.

11 DESCRIPTION

Dextrose Injection, USP 20%, 30%, 40%, 50% and 70% are sterile, nonpyrogenic, hypertonic solutions of Dextrose, USP in Water for Injection in a polyvinylchloride flexible plastic container for intravenous administration after appropriate admixture or dilution [see Dosage and Administration (2.1)].

Partial-fill containers, designed to facilitate admixture or dilution to provide dextrose in various concentrations, are available in various sizes. See Table 1 for the content and characteristics of these concentrated solutions. The solutions contain no bacteriostatic, antimicrobial agent or added buffer and are intended only for use as a single-dose injection following admixture or dilution. The pH is 4.3 (range is 3.2 to 6.5).

Water can permeate from inside the container into the overwrap but not in amounts sufficient to affect the solution significantly.

Table 1. Contents and Characteristics of Dextrose Injection 20%, 30%, 40%, 50%, and 70%
Strength | Fill Volume | Amount of Dextrose Hydrous per Container | kcal [Caloric value calculated on the basis of 3.4 kcal/g of dextrose, hydrous.] per Container | mOsmol per liter
20% (0.2 grams/mL) | 500 mL | 100 grams | 340 | 1009
30% (0.3 grams/mL) | 500 mL | 150 grams | 510 | 1514
40% (0.4 grams/mL) | 500 mL | 200 grams | 680 | 2018
50% (0.5 grams/mL) | 500 mL | 250 grams | 850 | 2523
70% (0.7 grams/mL) | 500 mL | 350 grams | 1190 | 3532

Dextrose, USP is chemically designated D-glucose, monohydrate (C6H12O6 • H2O), a hexose sugar freely soluble in water. The molecular weight of dextrose (D-glucose) monohydrate is 198.17. It has the following structural formula:

Dextrose may be derived from corn.

Water for Injection, USP is chemically designated H2O.

Dextrose Injection contains no more than 25 mcg/L of aluminum.

12 CLINICAL PHARMACOLOGY

12.1 Mechanism of Action

Dextrose Injection is used to supplement nutrition by providing glucose parenterally. Dextrose is oxidized to carbon dioxide and water, yielding energy.

16 HOW SUPPLIED/STORAGE AND HANDLING

Dextrose Injection, 20%, 30%, 40%, 50%, and 70% USP are sterile hypertonic solutions of dextrose supplied in single-dose, partial-fill flexible containers (see Tables 1 and 2) for intravenous administration after appropriate admixture or dilution [see Dosage and Administration (2.1)].

Do not remove container from the overwrap until intended for use.

Table 2: Strengths, Fill Volume, and NDC # of Dextrose Injection 20%, 30%, 40%, 50%, and 70%
Strength | Fill Volume | NDC#
20% (0.2 grams/mL) | 500 mL | 0409-7935-19 0990-7935-19
30% (0.3 grams/mL) | 500 mL | 0409-8004-15 0990-8004-15
40% (0.4 grams/mL) | 500 mL | 0409-7937-19 0990-7937-19
50% (0.5 grams/mL) | 500 mL | 0409-7936-19 0990-7936-19
70% (0.7 grams/mL) | 500 mL | 0409-7918-19 0990-7918-19

ICU Medical is transitioning NDC codes from the "0409" to a "0990" labeler code. Both NDC codes are expected to be in the market for a period of time.

Use the product immediately after mixing and the introduction of additives.

Store between 20°C to 25°C (68°F to 77°F). [See USP controlled room temperature.]

Do not freeze.

17 PATIENT COUNSELING INFORMATION

Inform patients, caregivers, or home healthcare providers of the following risks of Dextrose Injection:

- Hyperglycemia and hyperosmolar hyperglycemic state [see Warnings and Precautions (5.1)]
- Hypersensitivity reactions [see Warnings and Precautions (5.2)]
- Risk of infection [see Warnings and Precautions (5.3)]
- Vein damage and thrombosis [see Warnings and Precautions (5.5)]
- Aluminum toxicity [see Warnings and Precautions (5.6)]
- Risk of parenteral nutrition associated liver disease [see Warnings and Precautions (5.7)]
- Fluid overload and electrolyte imbalance [see Warnings and Precautions (5.8)]

EN-4695

ICU Medical, Inc., Lake Forest, Illinois, 60045, USA

PRINCIPAL DISPLAY PANEL - 70 g/100 mL Bag Label

500 mL
NDC 0990-7918-19

DEXTROSE
INJECTION,
USP

70%

IN 1000 mL PARTIAL-FILL CONTAINER
EACH 100 mL CONTAINS DEXTROSE, HYDROUS, USP
70 g IN WATER FOR INJECTION.
HYPERTONIC OSMOLARITY 3532 mOsmol/LITER (calc).
pH 4.3 (3.2 to 6.5)
SPECIFIC GRAVITY 1.236
CAUTION: HYPERTONIC. ADMINISTER ONLY AFTER
DILUTION VIA CENTRAL VENOUS CATHETER.
STERILE, NONPYROGENIC. SINGLE DOSE CONTAINER.
DOSAGE AND ADMINISTRATION: SEE PACKAGE
INSERT.
CAUTION: DO NOT USE UNLESS SOLUTION IS CLEAR,
CLOSURE IS INTACT, AND CONTAINER IS
UNDAMAGED. CHECK FOR MINUTE LEAKS BY
SQUEEZING FIRMLY. IF LEAKS ARE FOUND DISCARD
CONTAINER AND CONTENTS AS STERILITY MAY BE
IMPAIRED. MUST NOT BE USED IN SERIES
CONNECTIONS.

ADDITIVES MAY BE INCOMPATIBLE. CONSULT
WITH PHARMACIST, IF AVAILABLE. WHEN
INTRODUCING ADDITIVES, USE ASEPTIC
TECHNIQUE, MIX THOROUGHLY AND DO NOT
STORE.

RECOMMENDED STORAGE: ROOM TEMPERATURE
(25°C/77°F). AVOID EXCESSIVE HEAT. PROTECT FROM
FREEZING.
Rx ONLY

IM-4402

ICU Medical, Inc., Lake Forest, Illinois, 60045, USA

3
v
CONTAINS DEHP

70%

icumedical

PRINCIPAL DISPLAY PANEL - 70 g/100 mL Bag Overwrap

TO OPEN — TEAR AT NOTCH

The overwrap is a moisture and oxygen barrier. Do not remove
unit from overwrap until ready for use. Visually inspect
overwrap for tears or holes. Discard unit if overwrap is
damaged. Use unit promptly when pouch is opened. Store at
20 to 25°C (68 to 77°F). [See USP Controlled Room
Temperature.] Protect from freezing. See insert. After
removing the overwrap, check for minute leaks by squeezing
container firmly. If leaks are found, discard solution as sterility
may be impaired.

Rx only

WR-0551

ICU Medical, Inc., Lake Forest, Illinois, 60045, USA

icumedical

PRINCIPAL DISPLAY PANEL - 20 g/100 mL Bag Label

500 mL
IN 1000 mL PARTIAL-FILL CONTAINER

NDC 0990-7935-19

20% DEXTROSE
Injection, USP

EACH 100 mL CONTAINS DEXTROSE,
HYDROUS 20 g IN WATER FOR INJECTION.
1009 mOsmol/LITER (CALC.)
pH 4.3 (3.2 to 6.5)
CAUTION: HYPERTONIC. ADMINISTER
ONLY AFTER DILUTION. DEXTROSE
SOLUTIONS WITHOUT SALTS SHOULD
NOT BE USED IN BLOOD TRANSFUSIONS
BECAUSE OF POSSIBLE ROULEAU
FORMATION.

ADDITIVES MAY BE INCOMPATIBLE.
CONSULT WITH PHARMACIST, IF
AVAILABLE. WHEN INTRODUCING
ADDITIVES, USE ASEPTIC
TECHNIQUE, MIX THOROUGHLY AND
DO NOT STORE.

SINGLE-DOSE CONTAINER. FOR
INTRAVENOUS USE. USUAL DOSAGE:
SEE INSERT. STERILE, NONPYROGENIC.
USE ONLY IF SOLUTION IS CLEAR AND
CONTAINER IS UNDAMAGED. MUST
NOT BE USED IN SERIES CONNECTIONS.

Rx ONLY

3
v
CONTAINS DEHP

icumedical

IM-4404
ICU Medical, Inc., Lake Forest, Illinois, 60045, USA

PRINCIPAL DISPLAY PANEL - 20 g/100 mL Bag Overwrap

TO OPEN — TEAR AT NOTCH

The overwrap is a moisture and oxygen barrier. Do not remove
unit from overwrap until ready for use. Visually inspect
overwrap for tears or holes. Discard unit if overwrap is
damaged. Use unit promptly when pouch is opened.
Store at 20 to 25°C (68 to 77°F). [See USP Controlled Room
Temperature.] Protect from freezing. See insert. After removing
the overwrap, check for minute leaks by squeezing container
firmly. If leaks are found, discard solution as sterility may be
impaired.

Rx only

WR-0552

ICU Medical, Inc., Lake Forest, Illinois, 60045, USA

icumedical

PRINCIPAL DISPLAY PANEL - 50 g/100 mL Bag Label

500 mL
NDC 0990-7936-19

DEXTROSE
INJECTION,
USP

50%

IN 1000 mL PARTIAL-FILL CONTAINER
EACH 100 mL CONTAINS DEXTROSE, HYDROUS, USP
50 g IN WATER FOR INJECTION.
HYPERTONIC OSMOLARITY 2523 mOsmol/LITER (calc).
pH 4.3 (3.2 to 6.5)
SPECIFIC GRAVITY 1.170
CAUTION: HYPERTONIC. ADMINISTER ONLY AFTER
DILUTION VIA CENTRAL VENOUS CATHETER.
STERILE, NONPYROGENIC. SINGLE DOSE CONTAINER.
DOSAGE AND ADMINISTRATION: SEE PACKAGE
INSERT.
CAUTION: DO NOT USE UNLESS SOLUTION IS
CLEAR, CLOSURE IS INTACT, AND CONTAINER IS
UNDAMAGED. CHECK FOR MINUTE LEAKS BY
SQUEEZING FIRMLY. IF LEAKS ARE FOUND DISCARD
CONTAINER AND CONTENTS AS STERILITY MAY
BE IMPAIRED. MUST NOT BE USED IN SERIES
CONNECTIONS.

ADDITIVES MAY BE INCOMPATIBLE. CONSULT
WITH PHARMACIST, IF AVAILABLE. WHEN
INTRODUCING ADDITIVES, USE ASEPTIC
TECHNIQUE, MIX THOROUGHLY AND DO NOT
STORE.

RECOMMENDED STORAGE: ROOM TEMPERATURE
(25°C/77°F). AVOID EXCESSIVE HEAT. PROTECT FROM
FREEZING.

Rx ONLY

IM-4433
ICU Medical, Inc., Lake Forest, Illinois, 60045, USA

3
v
CONTAINS DEHP

50%

icumedical

PRINCIPAL DISPLAY PANEL - 50 g/100 mL Bag Overwrap

TO OPEN — TEAR AT NOTCH

The overwrap is a moisture and oxygen barrier. Do not remove
unit from overwrap until ready for use. Visually inspect
overwrap for tears or holes. Discard unit if overwrap is
damaged. Use unit promptly when pouch is opened. Store at
20 to 25°C (68 to 77°F). [See USP Controlled Room
Temperature.] Protect from freezing. See insert. After
removing the overwrap, check for minute leaks by squeezing
container firmly. If leaks are found, discard solution as sterility
may be impaired.

Rx only

WR-0555

ICU Medical, Inc., Lake Forest, Illinois, 60045, USA

icumedical

PRINCIPAL DISPLAY PANEL - 40 g/100 mL Bag Label

500 mL
IN 1000 mL PARTIAL-FILL CONTAINER

NDC 0990-7937-19

40% DEXTROSE
Injection, USP

EACH 100 mL CONTAINS DEXTROSE,
HYDROUS 40 g IN WATER FOR INJECTION.
2018 mOsmol/LITER (CALC.)
pH 4.3 (3.2 to 6.5)
CAUTION: HYPERTONIC. ADMINISTER ONLY
AFTER DILUTION VIA CENTRAL VENOUS
CATHETER. DEXTROSE SOLUTIONS
WITHOUT SALTS SHOULD NOT BE USED
IN BLOOD TRANSFUSIONS BECAUSE OF
POSSIBLE ROULEAU FORMATION.

ADDITIVES MAY BE INCOMPATIBLE.
CONSULT WITH PHARMACIST, IF
AVAILABLE. WHEN INTRODUCING
ADDITIVES, USE ASEPTIC TECHNIQUE,
MIX THOROUGHLY AND DO NOT STORE.

SINGLE-DOSE CONTAINER. FOR
INTRAVENOUS USE. USUAL DOSAGE: SEE
INSERT. STERILE, NONPYROGENIC. USE
ONLY IF SOLUTION IS CLEAR AND
CONTAINER IS UNDAMAGED. MUST NOT
BE USED IN SERIES CONNECTIONS.

Rx ONLY

3
v
CONTAINS DEHP

icumedical

IM-4434
ICU Medical, Inc., Lake Forest, Illinois, 60045, USA

PRINCIPAL DISPLAY PANEL - 40 g/100 mL Bag Overwrap

TO OPEN — TEAR AT NOTCH

The overwrap is a moisture and oxygen barrier. Do not remove
unit from overwrap until ready for use. Visually inspect
overwrap for tears or holes. Discard unit if overwrap is
damaged. Use unit promptly when pouch is opened. Store at
20 to 25°C (68 to 77°F). [See USP Controlled Room
Temperature.] Protect from freezing. See insert. After removing
the overwrap, check for minute leaks by squeezing container
firmly. If leaks are found, discard solution as sterility may be
impaired.

Rx only

WR-0557

ICU Medical, Inc., Lake Forest, Illinois, 60045, USA

icumedical

PRINCIPAL DISPLAY PANEL - 30 g/100 mL Bag Label

500 mL
IN 1000 mL PARTIAL-FILL CONTAINER

NDC 0990-8004-15

30% DEXTROSE
Injection, USP

EACH 100 mL CONTAINS DEXTROSE,
HYDROUS 30 g IN WATER FOR INJECTION.
1514 mOsmol/LITER (CALC.)
pH 4.3 (3.2 to 6.5)
CAUTION: HYPERTONIC. ADMINISTER
ONLY AFTER DILUTION VIA CENTRAL
VENOUS CATHETER. DEXTROSE
SOLUTIONS WITHOUT SALTS SHOULD
NOT BE USED IN BLOOD TRANSFUSIONS
BECAUSE OF POSSIBLE ROULEAU
FORMATION.

ADDITIVES MAY BE INCOMPATIBLE.
CONSULT WITH PHARMACIST, IF
AVAILABLE. WHEN INTRODUCING
ADDITIVES, USE ASEPTIC TECHNIQUE,
MIX THOROUGHLY AND DO NOT
STORE.

SINGLE-DOSE CONTAINER. FOR
INTRAVENOUS USE. USUAL DOSAGE:
SEE INSERT. STERILE, NONPYROGENIC.
USE ONLY IF SOLUTION IS CLEAR AND
CONTAINER IS UNDAMAGED. MUST
NOT BE USED IN SERIES CONNECTIONS.

Rx ONLY

3
v
CONTAINS DEHP

IM-4436
ICU Medical, Inc., Lake Forest, Illinois, 60045, USA

icumedical

PRINCIPAL DISPLAY PANEL - 30 g/100 mL Bag Overwrap

TO OPEN — TEAR AT NOTCH

The overwrap is a moisture and oxygen barrier. Do not remove
unit from overwrap until ready for use. Visually inspect
overwrap for tears or holes. Discard unit if overwrap is
damaged. Use unit promptly when pouch is opened. Store at
20 to 25°C (68 to 77°F). [See USP Controlled Room
Temperature.] Protect from freezing. See insert. After removing
the overwrap, check for minute leaks by squeezing container
firmly. If leaks are found, discard solution as sterility may be
impaired.

Rx only

WR-0560

ICU Medical, Inc., Lake Forest, Illinois, 60045, USA

icumedical